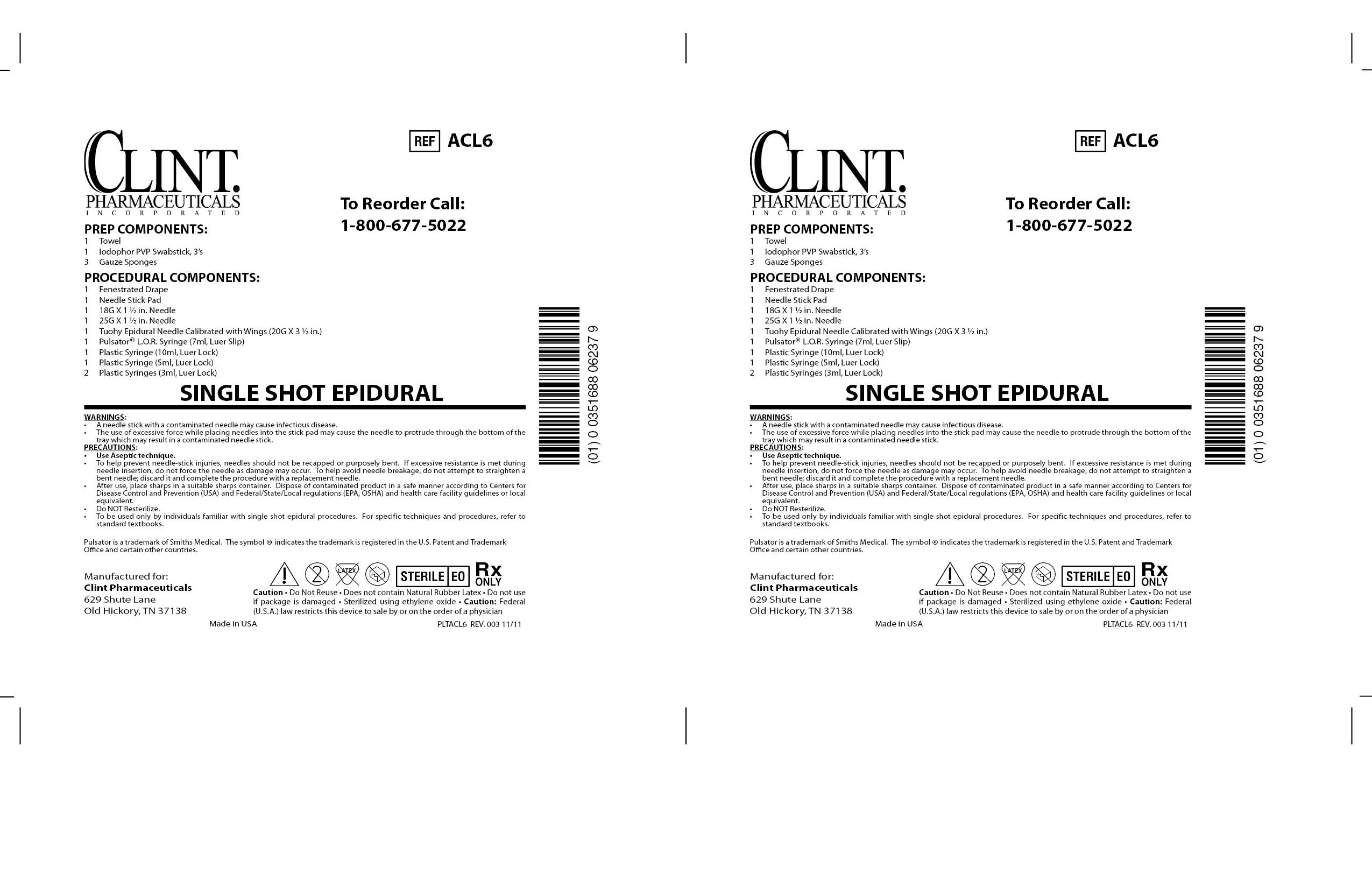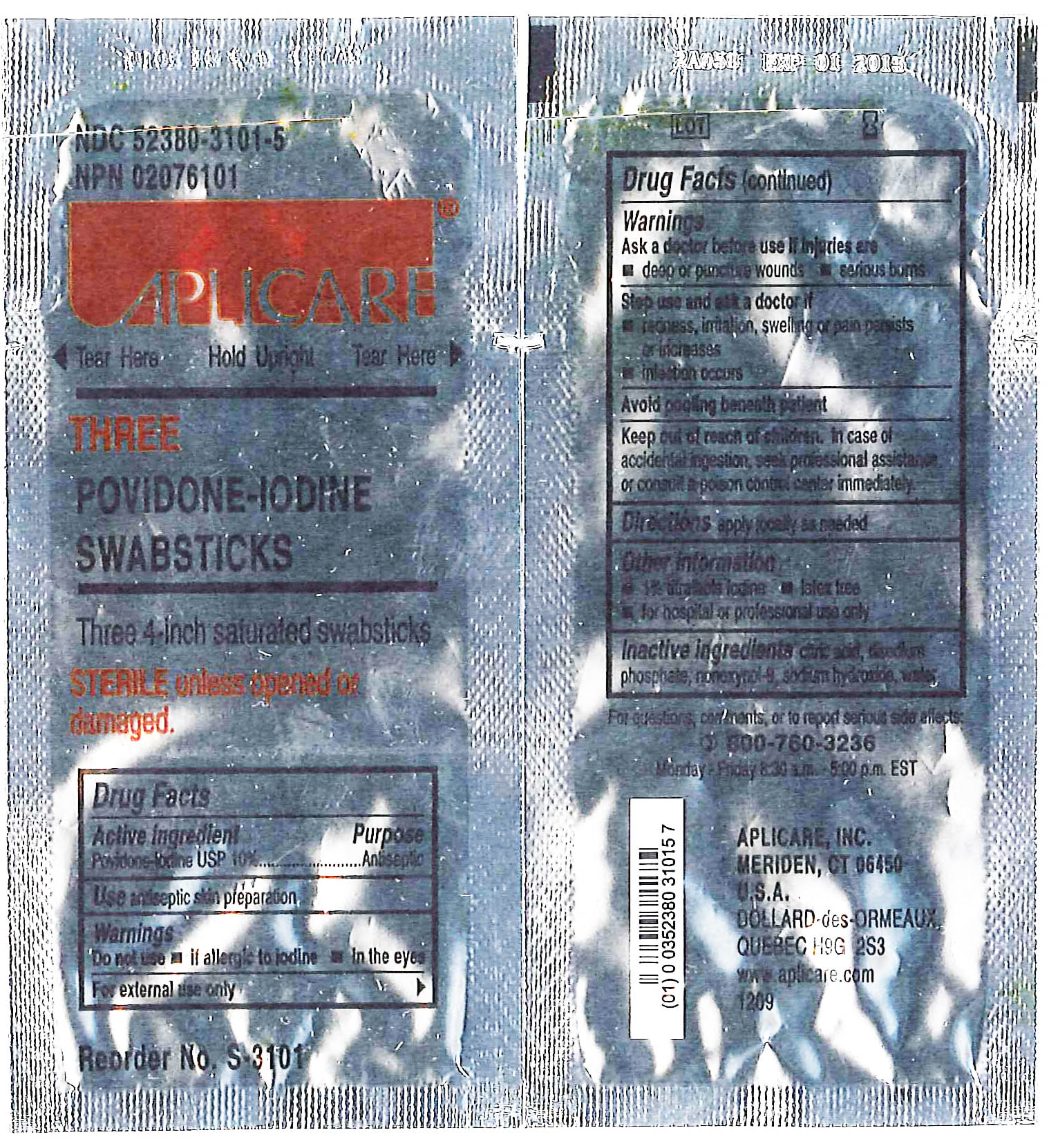 DRUG LABEL: ACL6 SINGLE SHOT EPIDURAL
NDC: 55553-450 | Form: KIT | Route: TOPICAL
Manufacturer: Clint Pharmaceuticals, Inc.
Category: other | Type: MEDICAL DEVICE
Date: 20120627

ACTIVE INGREDIENTS: POVIDONE-IODINE 9.8 g/96.4 mL
INACTIVE INGREDIENTS: SODIUM PHOSPHATE, DIBASIC; CITRIC ACID MONOHYDRATE; SODIUM HYDROXIDE; NONOXYNOL-9; WATER

Drug Facts

APLICARE THREE POVIDONE-IODINE SWABSTICKS
[Aplicare, Inc.]

Three 4-inch saturated swabsticks

Povidone-iodine 10%

Antiseptic

Warnings

Do not use

- if allergic to iodine
- in the eyes

For external use only

Ask a doctor before use if injuries are

- deep or puncture wounds
- serious burns

Stop use and ask a doctor if

- redness, irritation, swelling or pain persists or increases
- infection occurs

Avoid pooling beneath patient

Keep out of reach of children. In case of accidental ingestion, seek professional assistance or consult a poison control center immediately.

Package Label Display Panel